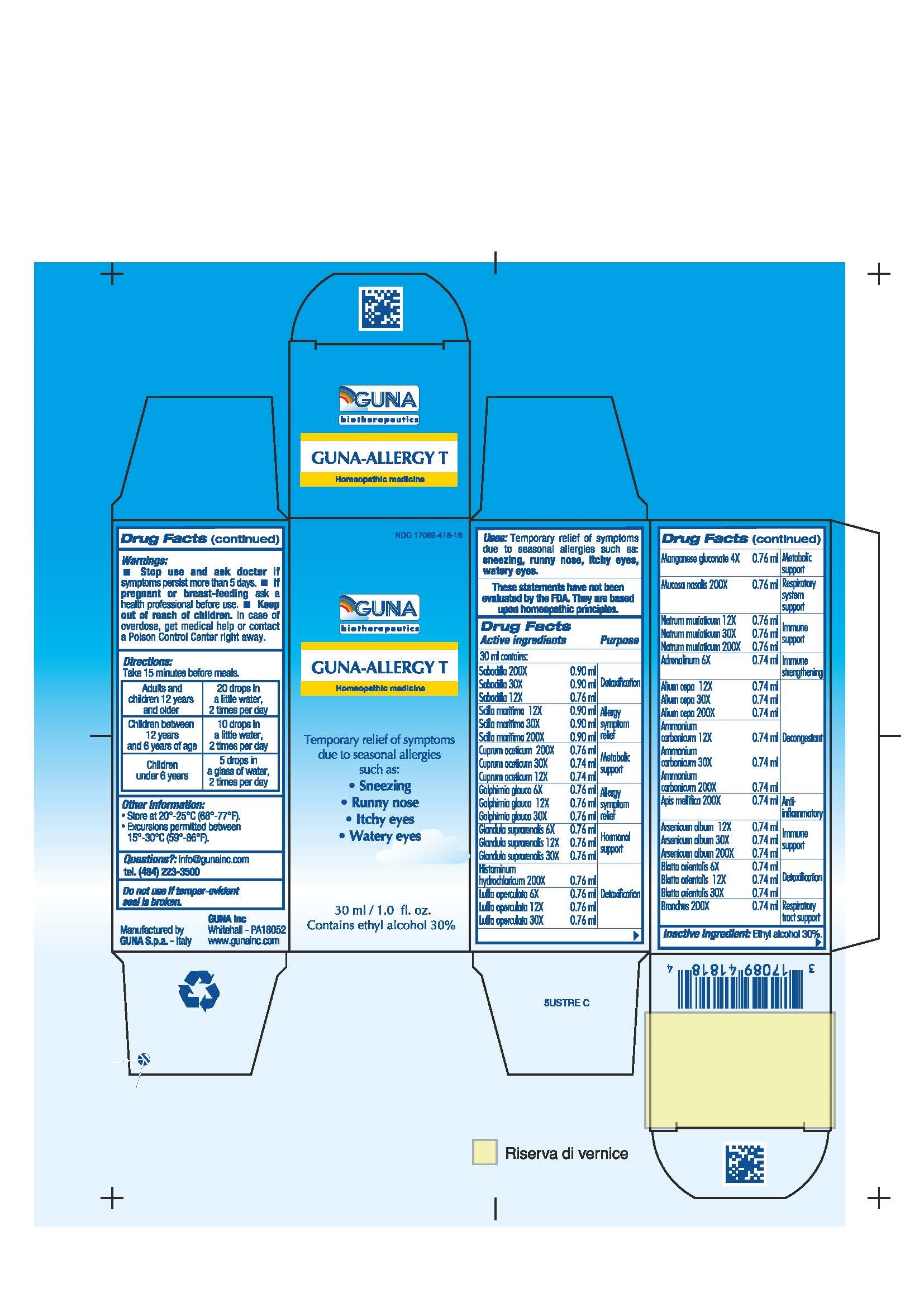 DRUG LABEL: GUNA-ALLERGY T
NDC: 17089-418 | Form: SOLUTION/ DROPS
Manufacturer: Guna spa
Category: homeopathic | Type: HUMAN OTC DRUG LABEL
Date: 20221115

ACTIVE INGREDIENTS: EPINEPHRINE 6 [hp_X]/30 mL; ONION 30 [hp_X]/30 mL; AMMONIUM CARBONATE 30 [hp_X]/30 mL; APIS MELLIFERA 200 [hp_X]/30 mL; ARSENIC TRIOXIDE 30 [hp_X]/30 mL; BLATTA ORIENTALIS 12 [hp_X]/30 mL; SUS SCROFA BRONCHUS 200 [hp_X]/30 mL; CUPRIC ACETATE 30 [hp_X]/30 mL; GALPHIMIA GLAUCA FLOWERING TOP 12 [hp_X]/30 mL; SUS SCROFA ADRENAL GLAND 12 [hp_X]/30 mL; HISTAMINE DIHYDROCHLORIDE 200 [hp_X]/30 mL; LUFFA OPERCULATA FRUIT 12 [hp_X]/30 mL; MANGANESE GLUCONATE 4 [hp_X]/30 mL; SUS SCROFA NASAL MUCOSA 200 [hp_X]/30 mL; SODIUM CHLORIDE 30 [hp_X]/30 mL; SCHOENOCAULON OFFICINALE SEED 30 [hp_X]/30 mL; DRIMIA MARITIMA BULB 30 [hp_X]/30 mL
INACTIVE INGREDIENTS: ALCOHOL 9 mL/30 mL

GUNA-ALLERGY T

ACTIVE INGREDIENTS/PURPOSE

ADRENALINUM 6X IMMUNE STRENGTHENING
ALIUM CEPA 12X 30X 200X DECONGESTANT
AMMONIUM CARBONICUM 12X 30X 200X DETOXIFICATION
APIS MELLIFICA 200X ANTI-INFLAMMATORY
ARSENICUM ALBUM 12X 30X 200X IMMUNE SUPPORT
BLATTA ORIENTALIS 6X 12X 30X DETOXIFICATION
BRONCHUS 200X RESPIRATORY TRACT SUPPORT
CUPRUM ACETICUM 12X 30X 200X METABOLIC SUPPORT
GALPHIMIA GLAUCA 6X 12X 30X ALLERGY SYMPTOM RELIEF
GLANDULA SUPRARENALIS 6X 12X 30X HORMONAL SUPPORT
HISTAMINUM HYDROCHLORICUM 200X DETOXIFICATION
LUFFA OPERCULATA 6X 12X 30X DETOXIFICATION
MANGANESE GLUCONATE 4X METABOLIC SUPPORT
MUCOSA NASALIS 200X RESPIRATORY SYSTEM SUPPORT
NATRUM MURIATICUM 12X 30X 200X IMMUNE SUPPORT
SABADILLA 12X 30X 200X DETOXIFICATION
SCILLA MARITIMA 12X 30X 200X ALLERGY SYMPTOM RELIEF

USES

Temporary relief of symptoms due to seasonal allergies such as:

- Sneezing
- Runny nose
- Itchy eyes
- Watery eyes

WARNINGS

- Stop use and ask doctor if symptoms persist more than 5 days.
- If pregnant or breast-feeding ask a health professional before use.
- Keep out of reach of children. In case of overdose, get medical help or contact a Poison Control Center right away.
- Contains ethyl alcohol 30%

PREGNANCY

If pregnant or breast-feeding ask a doctor before use

WARNINGS

Keep out of the reach of children

DIRECTIONS

Adults and children 12 years and older 20 drops in a little water 2 times per day
Children between 12 years and 6 years of age 10 drops in a little water 2 times per day
Children under 6 years 5 drops in a glass of water 2 times per day

QUESTIONS

Questions?: info@gunainc.com, tel. (484) 223-3500

INDICATIONS AND USAGE

Take 15 minutes before meals.

Inactive ingredient: Ethyl alcohol 30%.